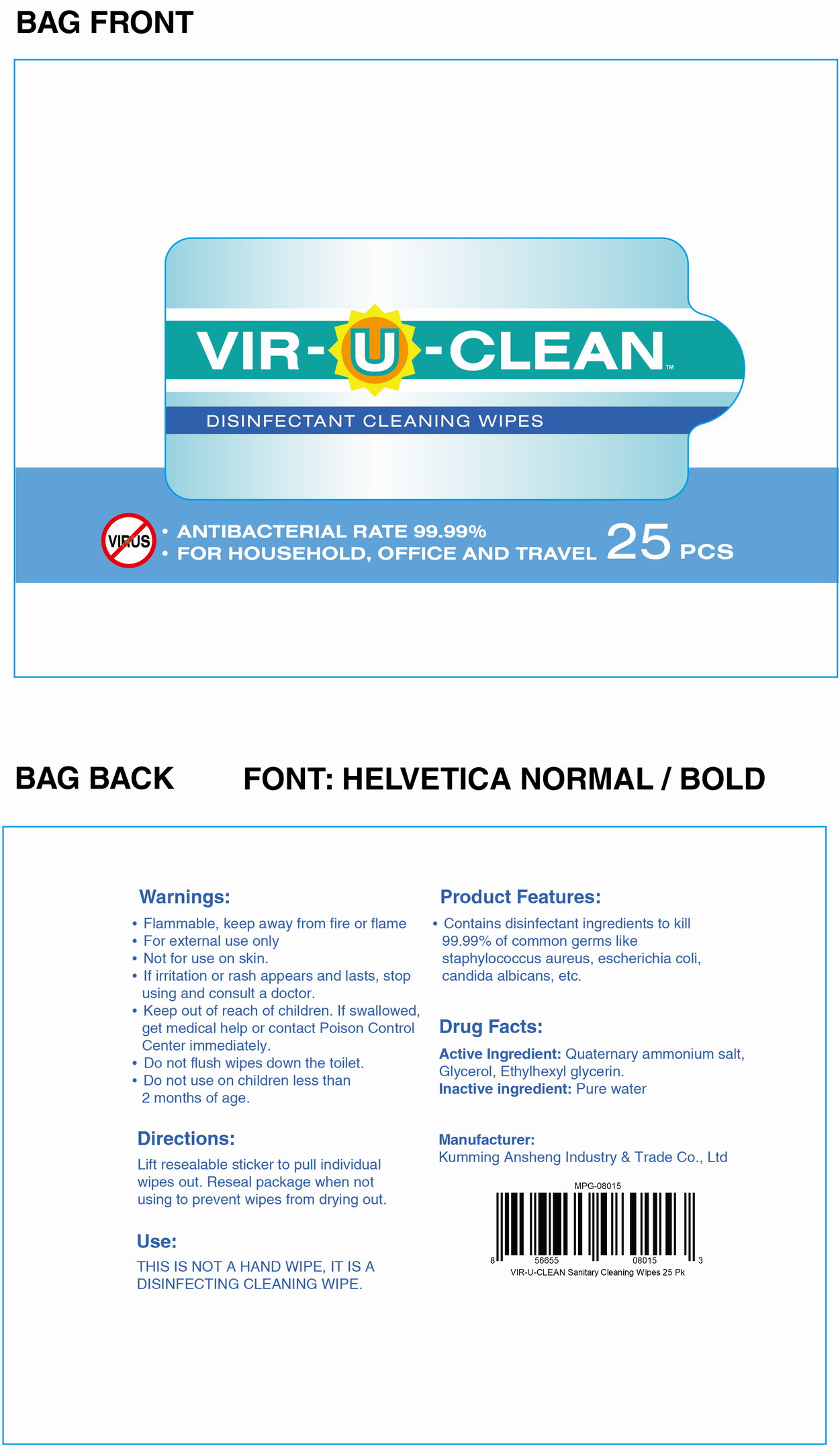 DRUG LABEL: VIR-U-CLEAN Disinfectant Cleaning Wipes
NDC: 78183-012 | Form: CLOTH
Manufacturer: Kunming Ansheng Industry & Trade Co., Ltd.
Category: otc | Type: HUMAN OTC DRUG LABEL
Date: 20201221

ACTIVE INGREDIENTS: BENZALKONIUM CHLORIDE 0.1 U/100 U; DIDECYLDIMONIUM CHLORIDE 0.2 U/100 U
INACTIVE INGREDIENTS: WATER; 2-ETHYLHEXYL GLYCIDYL ETHER 0.2 U/100 U; GLYCERIN 0.1 U/100 U

VIR-U-CLEAN DISIDFECTANT CLEANING WIPES

Active Ingredient(s)

Quaternary ammonium salt 0.2% v/v.

Purpose

To reduce bacteria for objects surface except human skin.

Use

THIS IS NOT A HAND WIPE, IT IS A DISINFECTING CLEANING WIPE.

Warnings

For external use only. Flammable. Keep away from fire or flame

Do not use

- Not for use on skin.
- Do not use on children less than 2 months of age.

STOP USE

If irritation or rash appears and lasts, stop using and consult a doctor.

Keep out of reach of children. If swallowed, get medical help or contact a Poison Control Center right away.

Directions

- Lift resealable sticker to pull individual wipes out.
- Reseal package when not using to prevent wipes from drying out.

Inactive ingredients

Glycerol, Ethylhexyl glycerin, Pure water

OTHER INFORMATION

- Dispose of wipe in the proper container after use.
- Do not flush down the toilet.
- Product Features: Contains disinfectant ingredients to kill 99.99% of common germs like staphylococcus aureus, escherichia coli,
  Candida albicans, etc.

Package Label - Principal Display Panel

25 wipes in 1 bag.

NDC: 78183-012-01;